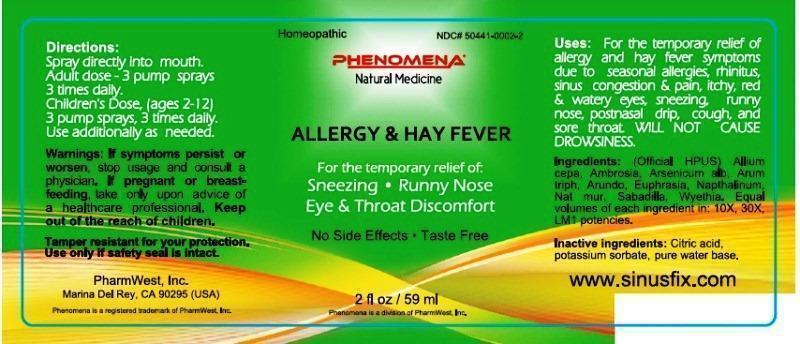 DRUG LABEL: Allergy and Hay Fever
NDC: 50441-0002 | Form: LIQUID
Manufacturer: PharmWest Inc.
Category: homeopathic | Type: HUMAN OTC DRUG LABEL
Date: 20140811

ACTIVE INGREDIENTS: ONION 10 [hp_X]/59 mL; AMBROSIA ARTEMISIIFOLIA 10 [hp_X]/59 mL; ARSENIC TRIOXIDE 10 [hp_X]/59 mL; ARISAEMA TRIPHYLLUM ROOT 10 [hp_X]/59 mL; ARUNDO PLINIANA ROOT 10 [hp_X]/59 mL; EUPHRASIA STRICTA 10 [hp_X]/59 mL; NAPHTHALENE 10 [hp_X]/59 mL; SODIUM CHLORIDE 10 [hp_X]/59 mL; SCHOENOCAULON OFFICINALE SEED 10 [hp_X]/59 mL; WYETHIA HELENIOIDES ROOT 10 [hp_X]/59 mL
INACTIVE INGREDIENTS: CITRIC ACID MONOHYDRATE; POTASSIUM SORBATE; WATER

Allergy & Hay Fever

ACTIVE INGREDIENT

Active Ingredients: (Official HPUS) Allium cepa, Ambrosia artemisiaefolia, Arsenicum album, Arum triphyllum, Arundo mauritanica, Euphrasia officinalis, Naphthalinum, Natrum muriaticum, Sabadilla, Wyethia helenioides. Equal volumes of each ingredient in 10X, 30X, LM1 potencies.

INACTIVE INGREDIENT

Inactive Ingredients: Citric acid, potassium sorbate, pure water base.

INDICATIONS AND USAGE

Uses: For the temporary relief of allergy and hay fever symptoms due to seasonal allergies, rhinitus, sinus congestion and pain, itchy, red and watery eyes, sneezing, runny nose, postnasal drip, cough and sore throat. Will not cause drowsiness.

DOSAGE AND ADMINISTRATION

Directions: Spray directly into mouth. Adult dose- 3 pump sprays 3 times daily. Children's Dose, (ages 2-12) 3 pump sprays, 3 times daily. Use additionally as needed.

WARNINGS

Warnings: If symptoms persist or worsen, stop usage and consult a physician. If pregnant or breast-feeding, take only upon advice of a healthcare professional.

Keep out of the reach of children.

OTHER SAFETY INFORMATION

Tamper resistant for your protection. Use only if safety seal is intact.

PURPOSE

Uses: For the temporary relief of allergy and hay fever symptoms due to

- seasonal allergies
- rhinitus
- sinus congestion and pain
- itchy, red and watery eyes
- sneezing
- runny nose
- postnasal drip
- cough
- sore throat

Will not cause drowsiness.